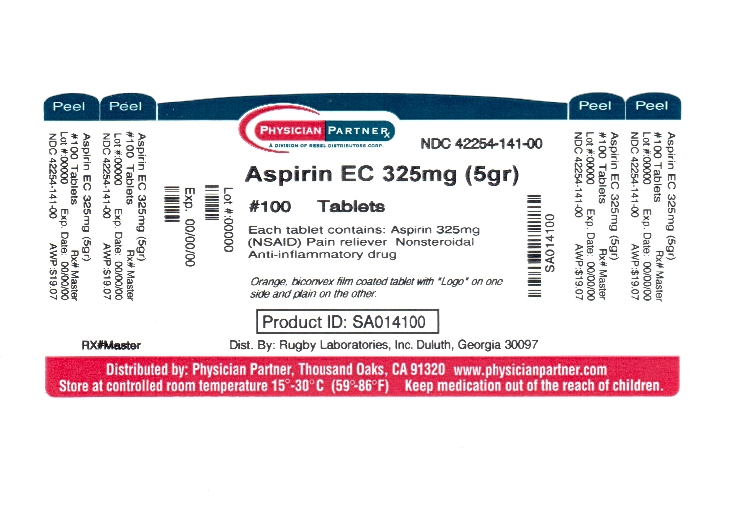 DRUG LABEL: Enteric Coated Aspirin
NDC: 42254-141 | Form: TABLET, DELAYED RELEASE
Manufacturer: Rebel Distributors Corp
Category: otc | Type: HUMAN OTC DRUG LABEL
Date: 20120209

ACTIVE INGREDIENTS: ASPIRIN 325 mg/1 1
INACTIVE INGREDIENTS: STARCH, CORN; CROSCARMELLOSE SODIUM; D&C YELLOW NO. 10; FD&C YELLOW NO. 6; HYPROMELLOSE 2910 (6 MPA.S); HYPROMELLOSE 2910 (15 MPA.S); METHACRYLIC ACID - ETHYL ACRYLATE COPOLYMER (1:1) TYPE A; CELLULOSE, MICROCRYSTALLINE; MINERAL OIL; POLYSORBATE 80; SILICON DIOXIDE; DIMETHICONE; SODIUM HYDROXIDE; SODIUM LAURYL SULFATE; TALC; TITANIUM DIOXIDE; TRIETHYL CITRATE

DRUG FACTS

Active ingredient (in each tablet)

Aspirin 325 mg (NSAID*)

*nonsteroidal anti-inflammatory drug

Purpose

Pain reliever

Uses

temporarily relieves

- headache
- muscle pain
- menstrual pain
- toothache
- minor pain of arthritis
- pain and fever of colds

Warnings
Reye's syndrome:

Children and teenagers who have or are recovering from chicken pox or flu-like symptoms should not use this product. When using this product, if changes in behavior with nausea and vomiting occur, consult a doctor because these symptoms could be an early sign of Reye's syndrome, a rare but serious illness.

Allergy alert:

Aspirin may cause a severe allergic reaction which may include

- hives
- shock
- facial swelling
- asthma (wheezing)

Stomach bleeding warning:

This product contains an NSAID, which may cause severe stomach bleeding. The chance is higher if the user

- has had stomach ulcers or bleeding problems
- takes a blood thinning (anticoagulant) or steroid drug
- takes other drugs containing prescription or nonprescription NSAIDs (aspirin, ibuprofen, naproxen, or others)
- takes more or for a longer time than directed
- has 3 or more alcoholic drinks every day while using this product
- is age 60 or older

Do not use

if you have ever had an allergic reaction to any other pain reliever/fever reducer

Ask a doctor before use if

- stomach bleeding warning applies to user
- user has a history of stomach problems such as heartburn
- user has high blood pressure, heart disease, liver cirrhosis, or kidney disease
- user is taking a diuretic
- user has asthma
- user has not been drinking fluids

Ask a doctor or pharmacist before use if user is

- taking a prescription drug for diabetes, gout, or arthritis
- taking any other drug
- under a doctor's care for any serious condition

Stop use and ask a doctor if

- user experiences any of the following signs of stomach bleeding:
  - feels faint
  - vomits blood
  - has bloody or black stools
  - has stomach pain that does not get better
- pain gets worse or lasts more than 10 days
- fever gets worse or lasts more than 3 days
- redness or swelling is present in the painful area
- any new symptoms appear
- ringing in the ears or a loss of hearing occurs

If pregnant or breast-feeding,

ask a health professional before use. It is especially important not to use aspirin during the last 3 months of pregnancy unless definitely directed to do so by a doctor because it may cause problems in the unborn child or complications during delivery.

Keep out of reach of children.

In case of overdose, get medical help or contact a Poison Control Center right away.

Directions

DRINK A FULL GLASS OF WATER WITH EACH DOSE

- adults and children 12 years and over: 1 - 2 tablets every 4 hours while symptoms last, not more than 12 tablets in 24 hours
- children under 12 years: ask a doctor

Other information

- store at 20° - 25°C (68° - 77°F)

Inactive ingredients

corn starch, croscarmellose sodium, D-C yellow #10 aluminum lake, FD-C yellow #6 aluminum lake, hypromellose, methacrylic acid copolymer, microcrystalline cellulose, mineral oil, polysorbate 80, simethicone, sodium hydroxide, sodium lauryl sulfate, talc, titanium dioxide, triethyl citrate

Questions or comments?

call

1-800-645-2158, 9 am - 5 pm ET, Monday - Friday